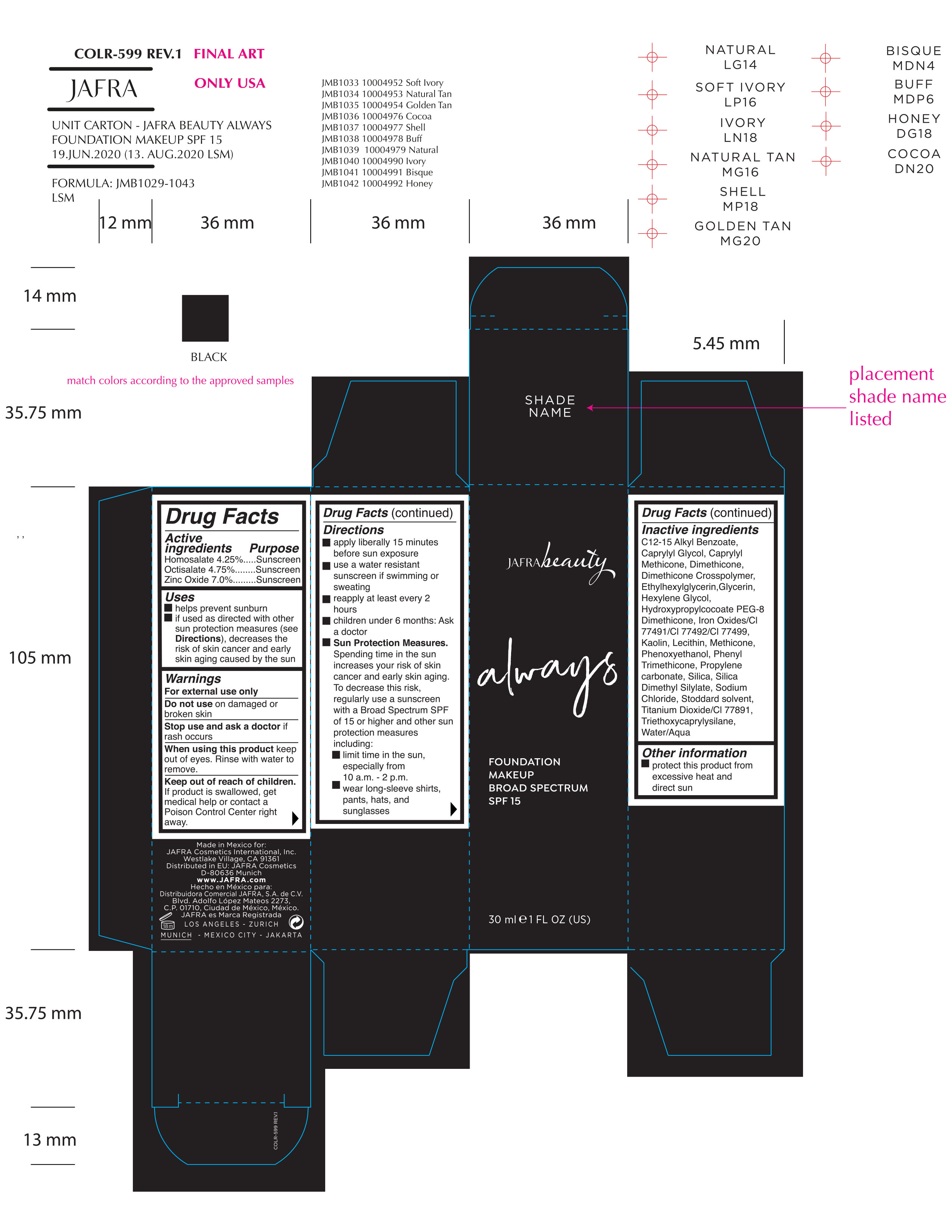 DRUG LABEL: Always Foundation Makeup Broad Spectrum SPF 15 Natural Tan
NDC: 68828-425 | Form: CREAM
Manufacturer: JAFRA COSMETICS INTERNATIONAL
Category: otc | Type: HUMAN OTC DRUG LABEL
Date: 20200825

ACTIVE INGREDIENTS: ZINC OXIDE 7 g/100 mL; HOMOSALATE 4.25 g/100 mL; OCTISALATE 4.75 g/100 mL
INACTIVE INGREDIENTS: CAPRYLYL GLYCOL; CAPRYLYL TRISILOXANE; METHICONE (20 CST); ETHYLHEXYLGLYCERIN; GLYCERIN; FERRIC OXIDE RED; LECITHIN, SOYBEAN; DIMETHICONE; PHENOXYETHANOL; PHENYL TRIMETHICONE; ALKYL (C12-15) BENZOATE; DIMETHICONE CROSSPOLYMER (450000 MPA.S AT 12% IN CYCLOPENTASILOXANE); HYDROXYPROPYLCOCOATE PEG-8 DIMETHICONE; FERRIC OXIDE YELLOW; FERROSOFERRIC OXIDE; KAOLIN; HEXYLENE GLYCOL; PROPYLENE CARBONATE; SILICA DIMETHYL SILYLATE; WHITE SPIRIT TYPE 1; TITANIUM DIOXIDE; WATER; SILICON DIOXIDE; SODIUM CHLORIDE; TRIETHOXYCAPRYLYLSILANE

Always Foundation Makeup Broad Spectrum SPF 15 Natural Tan

ACTIVE INGREDIENT

Homosalate 4.25% Purpose Sunscreen

Octisalate 4.75% Purpose Sunscreen

Zinc Oxide 7.0% Purpose Sunscreen

Uses

Helps prevent sunburn

If used as directed with other sun protection measures (see Directions), decreases the risk of skin cancer and early skin aging caused by the sun

Keep out of reach of children.

If product is swallowed, get medical help or contact a Poison Control Center right away.

Stop use and ask a doctor if rash occurs

WARNINGS

For external use only

Do not use on damaged or broken skin

Stop use and ask a doctor if rash occurs

When using this product keep out of eyes. Rinse with water to remove.

DOSAGE AND ADMINISTRATION

- Apply liberally 15 minutes before sun exposure
- Use a water resistant sunscreen if swimming or sweating
- Reapply at least every 2 hours
- Children under 6 months: Ask a doctor
- Sun Protection Measures. Spending time in the sun increases your risk of skin cancer and early skin aging. To decrease this risk, regularly use a sunscreen with a Broad Spectrum SPF of 15 or higher and other sun protection measures including:
- Limit time in the sun, especially from 10 a.m. – 2 p.m.
- Wear long-sleeve shirts, pants, hats, and sunglasses

INACTIVE INGREDIENT

C12-15 Alkyl Benzoate, Caprylyl Glycol, Caprylyl Methicone, Dimethicone, Dimethicone Crosspolymer, Ethylhexylglycerin, Glycerin, Hexylene Glycol, Hydroxypropylcocoate PEG-8 Dimethicone, Iron Oxides/CI 77491/CI 77492/CI 77499, Kaolin, Lecithin, Methicone, Phenoxyethanol, Phenyl Trimethicone, Propylene carbonate, Silica, Silica Dimethyl Silylate, Sodium Chloride, Stoddard solvent, Titanium Dioxide/CI 77891, Triethoxycaprylysilane, Water/Aqua

OTHER SAFETY INFORMATION

Protect this product from excessive heat and direct sun

PACKAGE LABEL

JAFRA beauty

Always

Foundation Makeup

Broad Spectrum SPF 15

30 ML e 1 FL OZ (US)